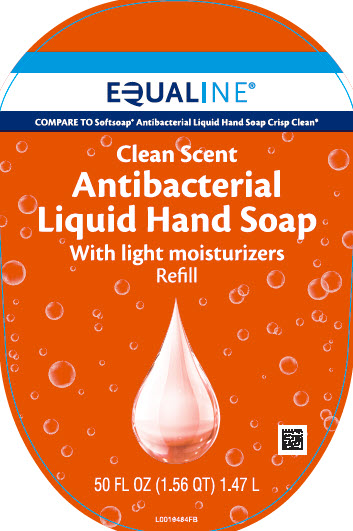 DRUG LABEL: Light Moisturizing Antibacterial
NDC: 41163-278 | Form: SOAP
Manufacturer: United Natural Foods, Inc. dba UNFI
Category: otc | Type: HUMAN OTC DRUG LABEL
Date: 20260217

ACTIVE INGREDIENTS: BENZALKONIUM CHLORIDE 1.3 mg/1 mL
INACTIVE INGREDIENTS: WATER; LAURAMINE OXIDE; COCAMIDOPROPYL BETAINE; LAURAMIDOPROPYLAMINE OXIDE; SODIUM CHLORIDE; MYRISTAMIDOPROPYLAMINE OXIDE; GLYCERIN; DISTEARETH-75 ISOPHORONE DIISOCYANATE; PEG-150 DISTEARATE; CITRIC ACID MONOHYDRATE; EDETATE SODIUM; SULISOBENZONE; SODIUM BENZOATE; D&C RED NO. 33; FD&C RED NO. 40; FD&C YELLOW NO. 5

Equaline 279.003/279AD
Light Moisturizing Antibacterial Hand Soap

Active ingredient

Benzalkonium chlroide 0.13%

Purpose

Antibacterial

Use

for handwashing to decrease bacteria on the skin

Warnings

For external use only: hands only

When using this product

avoid contact with eyes. If contact occurs, rinse eyes with water.

Stop use and ask a doctor if

- irritation or redness develop
- condition persists for more than 72 hours

Keep out of reach of children.

If swallowed, get medical help or contact a Poison Control Center right away.

Directions

- wet hands
- apply palmful to hands
- scrub thoroughly
- rinse thoroughly

Inactive ingredients

water, lauramine oxide, cocamidopropyl betaine, lauramidopropylamine oxide, sodium chloride, myristamidopropylamine oxide, glycerin, fragrance, disteareth-75 IPDI, PEG-150 distearate, citric acid, tetrasodium EDTA, benzophenone-4, sodium benzoate, red 33, red 40, yellow 5

*This product is not manufactured or distributed by Colgate-Palmolive Company, distributor of Softsoap Antibacterial Hand soap Crisp Clean.

Like it or let us make it right.

That's our quality promise.

855-423-2630

Distributed BY UNFI

PROVIDENCE, RI 02908 USA

Principal display panel

EQUALINE

COMPARE TO Softsoap Antibacterial Liquid Hand Soap Crisp Clean

Clean Scent Antibacterial Liquid Hand Soap

With light moisturizers

Refill

50 FL OZ (1.56 QT) 1.47 L